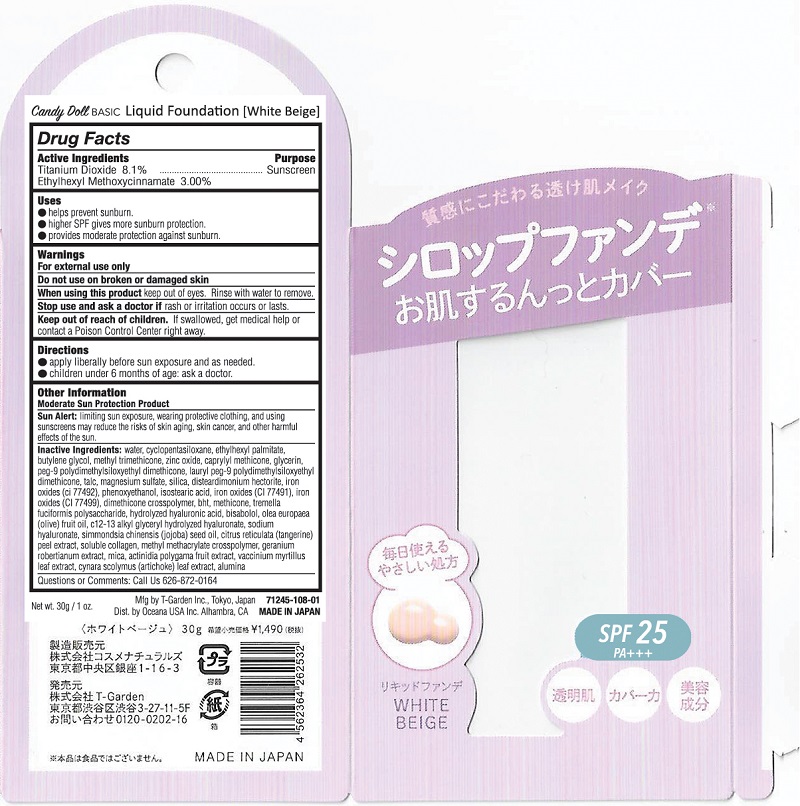 DRUG LABEL: Candy Doll Liquid Foundation
NDC: 71245-108 | Form: LIQUID
Manufacturer: T-Garden Inc
Category: otc | Type: HUMAN OTC DRUG LABEL
Date: 20170320

ACTIVE INGREDIENTS: TITANIUM DIOXIDE 2.43 g/30 g; OCTINOXATE 0.9 g/30 g
INACTIVE INGREDIENTS: WATER; GLYCERIN; BROWN IRON OXIDE

Candy Doll Liquid Foundation

Active Ingredients

Titanium Dioxide 8.1%

Ethylhexyl Methoxycinammate 3.0%

Purpose

Sunscreen

Warnings

For external use only

Do not use on broken or damaged skin

When Using

When using this product keep out of eyes. Rinse with water to remove.

Stop use and ask a doctor if rash or irritation occurs or lasts.

Keep Out of Reach of Children

Directions

apply liberally before sun exposure and as needed

children under 6 months of age: ask a doctor

Inactive Ingredients

water, cyclopentasiloxane, glycerin, cetyl ethylhexanoate, butylene glycol, diphenylsiloxy phenyl tremethicone, methyl methacrylate crosspolymer, PEG-10 dimethicone, sorbitan sesquiisostearate, magnesium sulfate, sorbitan sesquioleate, cetyl PEG/PPG-10/1 dimethicone, disteardimonium hectorite, alumina, aluminum hydroxide, glyceryl behenate/eicosadioate, stearic acid, talc, ethylhexylglycerin, phenoxyethanol, dimethicone, propylene carbonate, mica, hydrogen dimethicone, ultramarines, iron oxides, polyquaternium-51, carmine, tin oxide, sodium hyaluronate, aloe barbadensis leaf extract, cocos nucifera (coconut) oil, royal jelly extract

Questions

Questions or Comments: Call Us 626-872-0164

PDP Image

CandyDoll_PureLiquidFoundation_108-01 (1).jpg